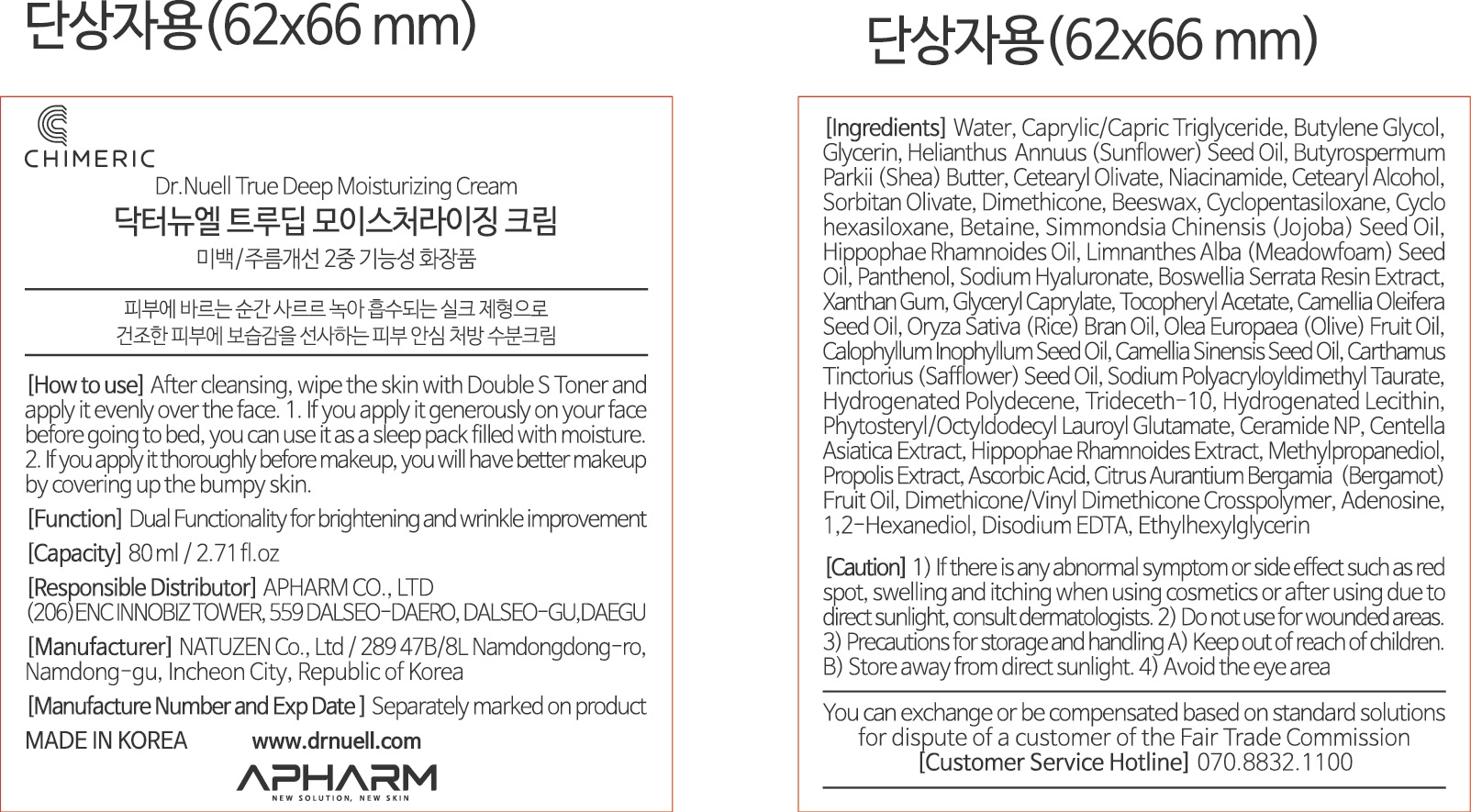 DRUG LABEL: Dr.NUELL True Deep Mosturizing
NDC: 73430-0003 | Form: CREAM
Manufacturer: Apharm Co., Ltd.
Category: otc | Type: HUMAN OTC DRUG LABEL
Date: 20191103

ACTIVE INGREDIENTS: GLYCERIN 5.105 g/100 mL
INACTIVE INGREDIENTS: ADENOSINE; BUTYLENE GLYCOL

ACTIVE INGREDIENT

glycerin

PURPOSE

dual functionality for brightening and wrinkle improvement certified

Keep out of reach of children

INDICATIONS AND USAGE

after cleansing, wipe the skin with double s toner and apply it evenly over the face

WARNINGS

1) if there is any abnormal symptom or side effect, such as red spot, swelling and itching when using cosmetlcs or after using due to direct sunlight, consult dermatologists
2) Do not use for wounded areas
3) Precautions for storage and handling
keep out of reach of children, store away from direct sunlight
4) avoid the eye area

INACTIVE INGREDIENT

water, butylene glycol, 1,2-hexanediol, dimethicone, etc

DOSAGE AND ADMINISTRATION

For external use only